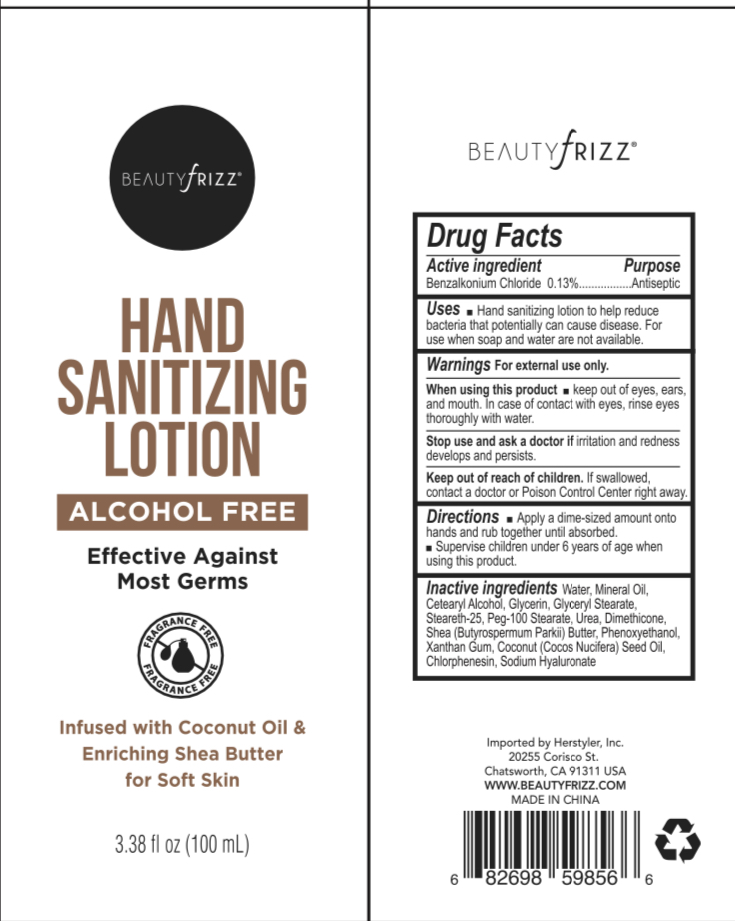 DRUG LABEL: Hand Sanitizer
NDC: 76383-030 | Form: LOTION
Manufacturer: BBC GROUP LIMITED
Category: otc | Type: HUMAN OTC DRUG LABEL
Date: 20200523

ACTIVE INGREDIENTS: BENZALKONIUM CHLORIDE 1.3 mg/1 mL
INACTIVE INGREDIENTS: HYALURONATE SODIUM; COCONUT OIL; CHLORPHENESIN; CETOSTEARYL ALCOHOL; GLYCERIN; GLYCERYL MONOSTEARATE; STEARETH-25; PEG-100 STEARATE; WATER; UREA; DIMETHICONE; SHEA BUTTER; PHENOXYETHANOL; XANTHAN GUM; MINERAL OIL

Beautyfrizz Hand Sanitizer Lotion bzk Coconut

Active Ingredient

Benzalkonium Chloride 0.13%

Purpose

Antiseptic

Uses

■ Hand sanitizing lotion to help reduce bacteria that potentially can cause disease. For use when soap and water are not available.

Warnings

For external use only.

When using this product

■ keep out of eyes, ears, and mouth. In case of contact with eyes, rinse eyes throughly with water.

Stop use and ask a doctor if

irritation and redness develops and persists.

Keep out of reach of children

If swallowed, contact a doctor or Poison Control Center right away.

Directions

■ Apply a dime-sized amount onto hands and rub together until absorbed. ■ Supervise children under 6 years of age when using this product

Inactive ingredients

Water, Mineral Oil, Cetearyl Alcohol, Glycerin, Glyceryl Stearate, Steareth-25, PEG-100 Stearate, Urea, Dimethicone, Shea (Butyrospermum Parkii) Butter, Phenoxyethanol, Xanthan Gum, Coconut (Cocos Nucifera) Seed Oil, Chlorphenesin, Sodium Hyaluronate